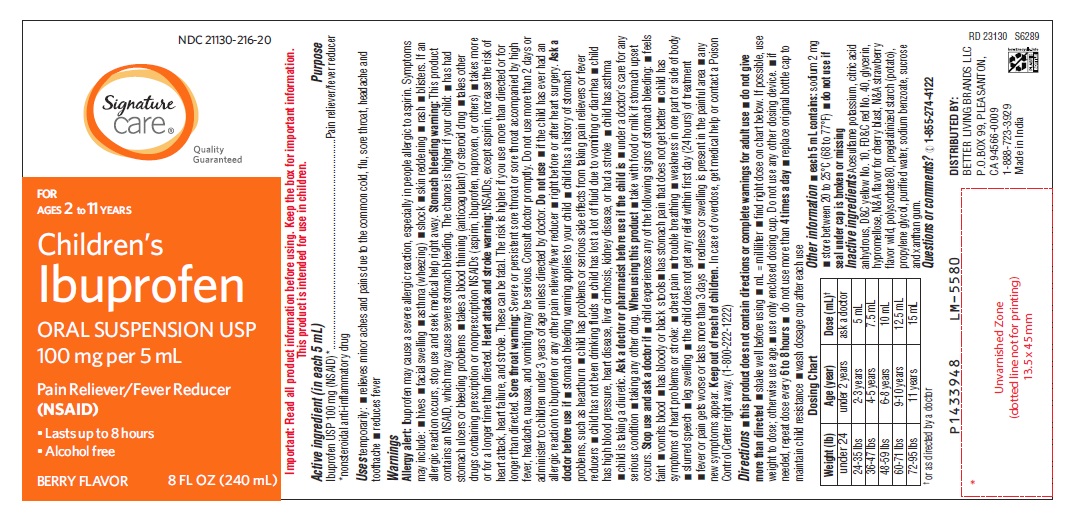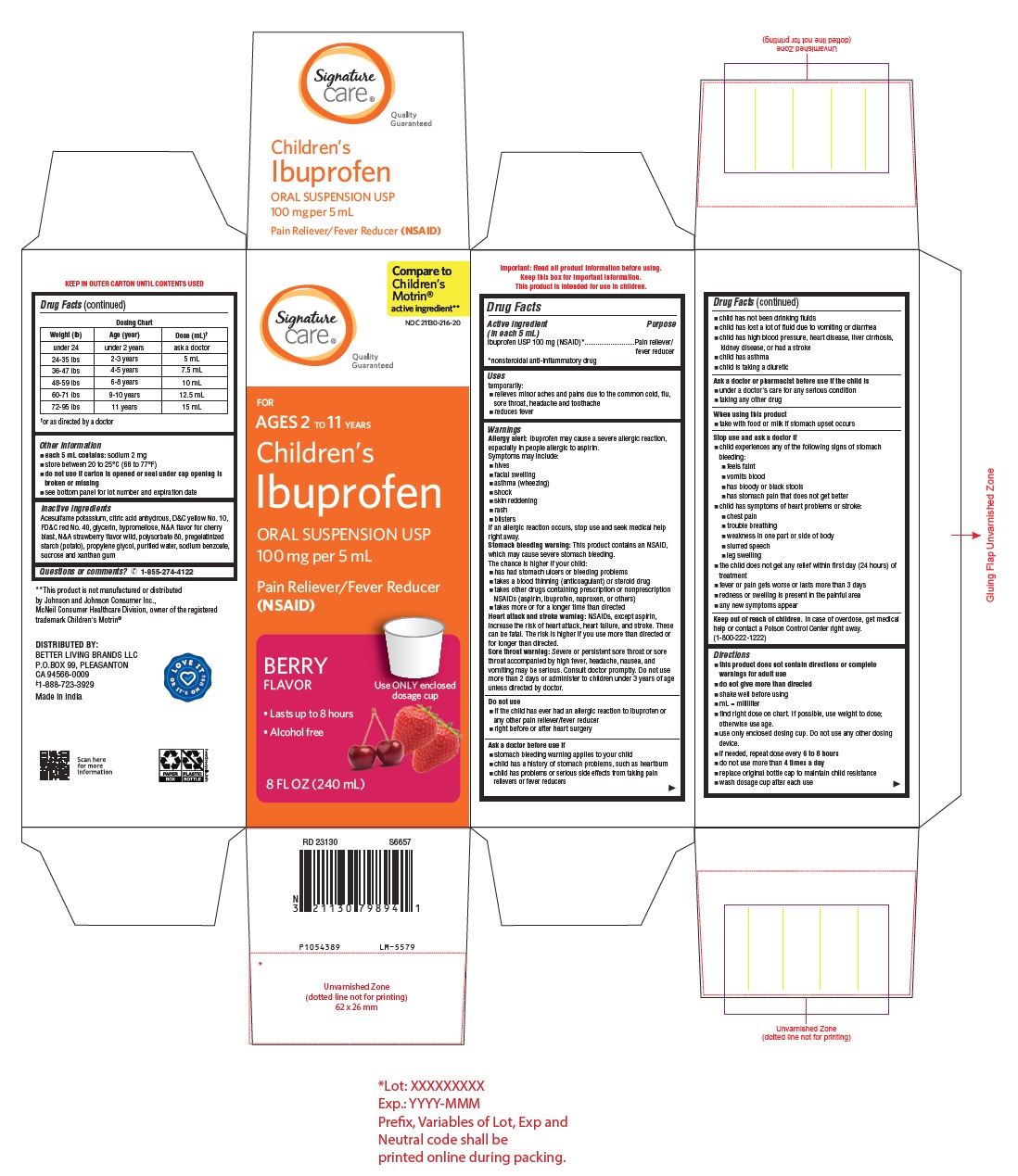 DRUG LABEL: CHILDRENS IBUPROFEN
NDC: 21130-216 | Form: SUSPENSION
Manufacturer: Better Living Brands, LLC
Category: otc | Type: Human OTC Drug Label
Date: 20250902

ACTIVE INGREDIENTS: IBUPROFEN 100 mg/5 mL
INACTIVE INGREDIENTS: ACESULFAME POTASSIUM; STARCH, POTATO; PROPYLENE GLYCOL; WATER; SODIUM BENZOATE; SUCROSE; XANTHAN GUM; ANHYDROUS CITRIC ACID; D&C YELLOW NO. 10; FD&C RED NO. 40; GLYCERIN; HYPROMELLOSE 2208 (4000 MPA.S); CHERRY; STRAWBERRY; POLYSORBATE 80

Drug Facts

Active ingredient (in each 5 mL)

Ibuprofen USP 100 mg (NSAID)*

Purpose

Pain reliever/fever reducer

*nonsteroidal anti-inflammatory drug

Uses

temporarily:

- relieves minor aches and pains due to the common cold, flu, sore throat, headache and toothache
- reduces fever

Warnings

Allergy alert: Ibuprofen may cause a severe allergic reaction, especially in people allergic to aspirin. Symptoms may include:

- hives
- facial swelling
- asthma (wheezing)
- shock
- skin reddening
- rash
- blisters

If an allergic reaction occurs, stop use and seek medical help right away.

Stomach bleeding warning: This product contains an NSAID, which may cause severe stomach bleeding. The chance is higher if your child:

- has had stomach ulcers or bleeding problems
- takes a blood thinning (anticoagulant) or steroid drug
- takes other drugs containing prescription or nonprescription NSAIDs (aspirin, ibuprofen, naproxen, or others)
- takes more or for a longer time than directed

Heart attack and stroke warning: NSAIDs, except aspirin, increase the risk of heart attack, heart failure, and stroke. These can be fatal. The risk is higher if you use more than directed or for longer than directed.

Sore throat warning: Severe or persistent sore throat or sore throat accompanied by high fever, headache, nausea, and vomiting may be serious. Consult doctor promptly. Do not use more than 2 days or administer to children under 3 years of age unless directed by doctor.

Do not use

- if the child has ever had an allergic reaction to ibuprofen or any other pain reliever/fever reducer
- right before or after heart surgery

Ask a doctor before use if

- stomach bleeding warning applies to your child
- child has a history of stomach problems, such as heartburn
- child has problems or serious side effects from taking pain relievers or fever reducers
- child has not been drinking fluids
- child has lost a lot of fluid due to vomiting or diarrhea
- child has high blood pressure, heart disease, liver cirrhosis, kidney disease, or had a stroke
- child has asthma
- child is taking a diuretic

Ask a doctor or pharmacist before use if the child is

- under a doctor's care for any serious condition
- taking any other drug

When using this product

- take with food or milk if stomach upset occurs

Stop use and ask a doctor if

- child experiences any of the following signs of stomach bleeding:

• feels faint

• vomits blood

• has bloody or black stools

• has stomach pain that does not get better

- child has symptoms of heart problems or stroke:

• chest pain

• trouble breathing

• weakness in one part or side of body

• slurred speech

• leg swelling

- the child does not get any relief within first day (24 hours) of treatment
- fever or pain gets worse or lasts more than 3 days
- redness or swelling is present in the painful area
- any new symptoms appear

Keep out of reach of children.

In case of overdose, get medical help or contact a Poison Control Center right away. (1-800-222-1222)

Directions

- this product does not contain directions or complete warnings for adult use
- do not give more than directed
- shake well before using
- mL = milliliter
- find right dose on chart. If possible, use weight to dose; otherwise use age.
- use only enclosed dosing cup. Do not use any other dosing device.
- if needed, repeat dose every 6 to 8 hours
- do not use more than 4 times a day
- replace original bottle cap to maintain child resistance
- wash dosage cup after each use

Dosing Chart
Weight (lb) | Age (year) | Dose (mL)†
under 24 | under 2 years | ask a doctor
24-35 lbs | 2-3 years | 5 mL
36-47 lbs | 4-5 years | 7.5 mL
48-59 lbs | 6-8 years | 10 mL
60-71 lbs | 9-10 years | 12.5 mL
72-95 lbs | 11 years | 15 mL
† or as directed by a doctor

Other information

- each 5 mL contains: sodium 2 mg
- store between 20 to 25°C (68 to 77°F)
- do not use if carton is opened or seal under cap opening is broken or missing
- see bottom panel for lot number and expiration date

Inactive ingredients

Acesulfame potassium, citric acid anhydrous, D&C yellow No. 10, FD&C red No. 40, glycerin, hypromellose, N&A flavor for cherry blast, N&A strawberry flavor wild, polysorbate 80, pregelatinized starch (potato), propylene glycol, purified water, sodium benzoate, sucrose and xanthan gum

Questions or comments?

Call 1-855-274-4122

DISTRIBUTED BY:

BETTER LIVING BRANDS LLC

P.O.BOX 99, PLEASANTON

CA 94566-0009

‡1-888-723-3929

Made in India

PACKAGE LABEL-PRINCIPAL DISPLAY PANEL 8 FL OZ (240 mL) Container Label

NDC 21130-216-20

Signature

care®

Quality

Guranteed

FOR

AGES 2 to 11 YEARS

Children’s

Ibuprofen

ORAL SUSPENSION USP

100 mg per 5 mL

Pain Reliever/Fever Reducer

(NSAID)

• Lasts up to 8 hours

• Alcohol free

BERRY FLAVOR

8 FL OZ (240 mL)

PACKAGE LABEL-PRINCIPAL DISPLAY PANEL 8 FL OZ (240 mL) Carton Label

Compare to

Children's Motrin®

active ingredient**

NDC 21130-216-20

Signature

care®

Quality

Guranteed

FOR

AGES 2 TO 11 YEARS

Children’s

Ibuprofen

ORAL SUSPENSION USP

100 mg per 5 mL

Pain Reliever/Fever Reducer

(NSAID)

BERRY

FLAVOR

• Lasts up to 8 hours

• Alcohol free

Use ONLY enclosed

dosage cup

8 FL OZ (240 mL)